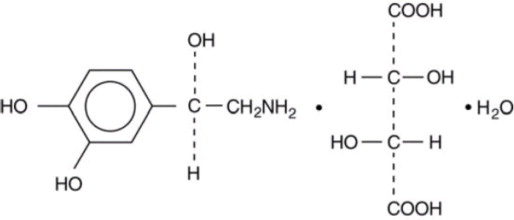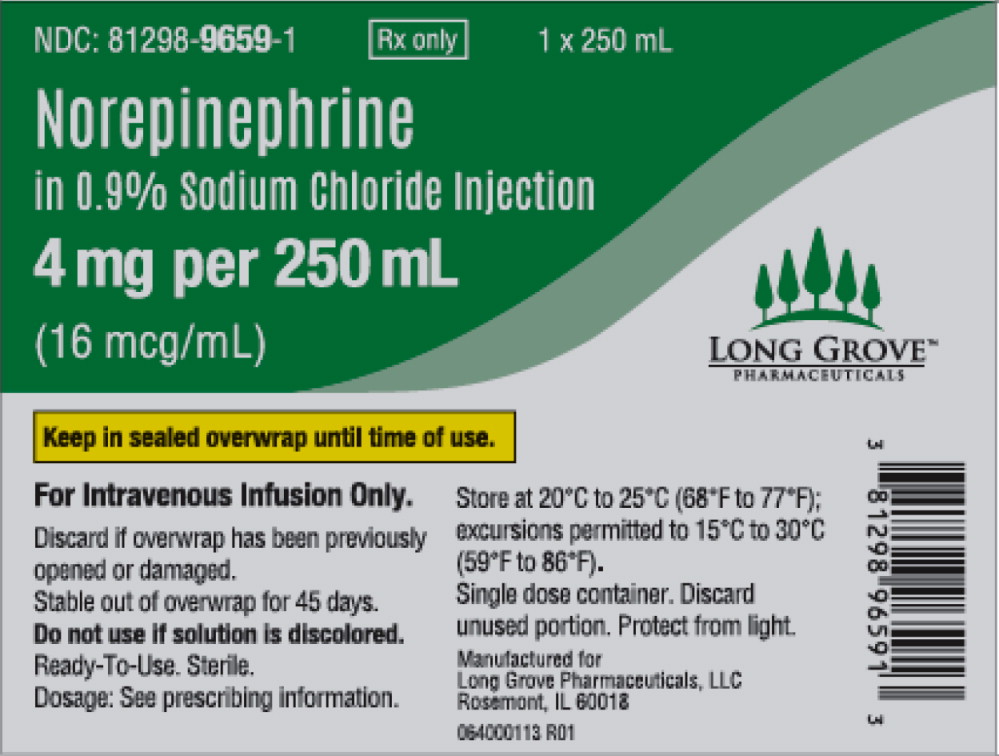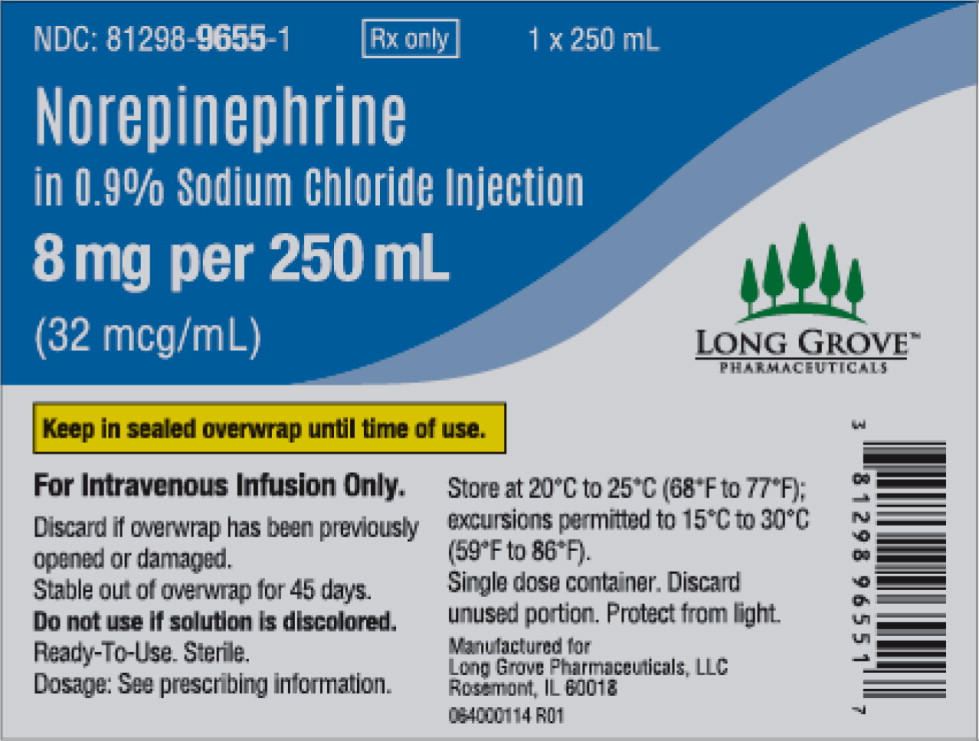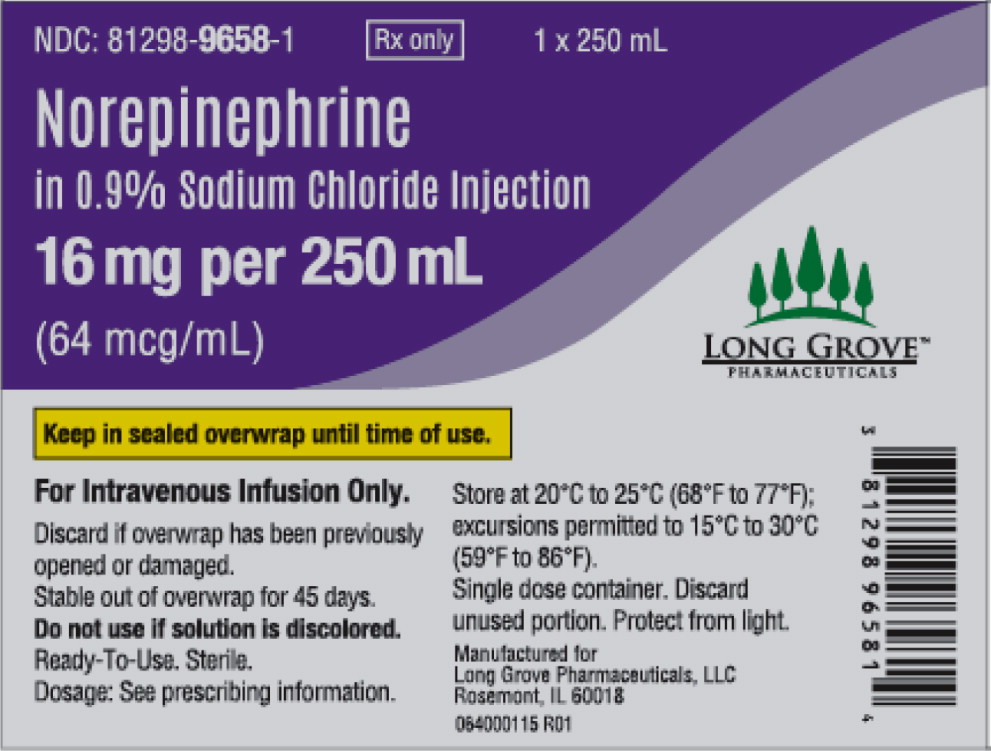 DRUG LABEL: Norepinephrine
NDC: 81298-9659 | Form: SOLUTION
Manufacturer: Long Grove Pharmaceuticals, LLC
Category: prescription | Type: HUMAN PRESCRIPTION DRUG LABEL
Date: 20251204

ACTIVE INGREDIENTS: NOREPINEPHRINE BITARTRATE 16 ug/1 mL
INACTIVE INGREDIENTS: EDETATE DISODIUM; SODIUM CHLORIDE; HYDROCHLORIC ACID; SODIUM HYDROXIDE; WATER

HIGHLIGHTS OF PRESCRIBING INFORMATION

These highlights do not include all the information needed to use NOREPINEPHRINE IN SODIUM CHLORIDE INJECTION safely and effectively. See full prescribing information for NOREPINEPHRINE IN SODIUM CHLORIDE INJECTION.
NOREPINEPHRINE IN SODIUM CHLORIDE INJECTION, for intravenous use
Initial U.S. Approval: 1950

1 INDICATIONS AND USAGE

Norepinephrine in Sodium Chloride Injection is a catecholamine indicated for restoration of blood pressure in adult patients with acute hypotensive states. (1)

2 DOSAGE AND ADMINISTRATION

- No further dilution prior to infusion is required (2.1)
- Initial intravenous infusion rate of 8 to 12 mcg per minute, adjust the rate of flow to establish and maintain a low to normal blood pressure (usually 80 to 100 mm Hg) sufficient to maintain the circulation of vital organs (2.2)
- The average maintenance dose ranges from 2 to 4 mcg per minute. (2.2)

3 DOSAGE FORMS AND STRENGTHS

- Injection: in a single dose infusion bags with
  - 4 mg/250 mL (16 mcg/mL) of norepinephrine in 0.9% Sodium Chloride
  - 8 mg/250 mL (32 mcg/mL) of norepinephrine in 0.9% Sodium Chloride
  - 16 mg/250 mL (64 mcg/mL) of norepinephrine in 0.9% Sodium Chloride

4 CONTRAINDICATIONS

- None. (4)

5 WARNINGS AND PRECAUTIONS

- Tissue Ischemia: Avoid extravasation into tissues, which can cause local necrosis (5.1)
- Hypotension After Abrupt Discontinuation: Sudden cessation of the infusion rate may result in marked hypotension. Reduce the Norepinephrine in Sodium Chloride Injection infusion rate gradually. (5.2)
- Cardiac Arrhythmias: Norepinephrine in Sodium Chloride Injection may cause arrhythmias. Monitor cardiac function in patients with underlying heart disease. (5.3)

6 ADVERSE REACTIONS

Most common adverse reactions are ischemic injury, bradycardia, anxiety, transient headache, respiratory difficulty, and extravasation necrosis at injection site. (6)

To report SUSPECTED ADVERSE REACTIONS, contact Long Grove Pharmaceuticals LLC at 1-855-642-2594 or FDA at 1-800-FDA-1088 or www.fda.gov/medwatch.

7 DRUG INTERACTIONS

- Monoamine oxidase inhibitors (MAOI) or antidepressants of the triptyline or imipramine types may result in hypertension. (7.1)
- Cyclopropane and halothane anesthetics increase cardiac autonomic irritability. (7.4)

8 USE IN SPECIFIC POPULATIONS

- Elderly patients may be at greater risk of developing adverse reactions. (8.5)

FULL PRESCRIBING INFORMATION

1 INDICATIONS AND USAGE

Norepinephrine in Sodium Chloride Injection is indicated to raise blood pressure in adult patients with severe, acute hypotension.

2 DOSAGE AND ADMINISTRATION

2.1 Important Dosage and Administration Instructions

Correct Hypovolemia

Address hypovolemia before initiation of Norepinephrine in Sodium Chloride Injection therapy. If the patient does not respond to therapy, suspect occult hypovolemia [see Warnings and Precautions (5.1)].

Administration

Infuse Norepinephrine in Sodium Chloride Injection into a large vein. Avoid infusions into the veins of the leg in the elderly or in patients with occlusive vascular disease of the legs [see Warnings and Precautions (5.1)]. Avoid using a catheter-tie-in technique.

Inspect parenteral drug products for particulate matter and discoloration prior to use, whenever solution and container permit.

Do not open the aluminum foil pouch until time of use. The premixed, ready-to-use infusion bag has a single port for insertion of the infusion set only. Do not use this port to remove content from the bag or add another medication. Once the infusion bag has been connected to the infusion set, it is stable for 24 hours for intermittent or continuous use, as long as the bag stays connected to the infusion set.

Discontinuation

When discontinuing the infusion, reduce the flow rate gradually. Avoid abrupt withdrawal. Single dose only. Discard unused portion.

2.2 Dosage

After an initial dose of 8 to 12 mcg per minute via intravenous infusion, assess patient response and adjust dosage to maintain desired hemodynamic effect. Monitor blood pressure every two minutes or continuously until the desired hemodynamic effect is achieved, and then monitor blood pressure every five minutes for the duration of the infusion.

Recommended Average Maintenance Dosage:

Typical maintenance intravenous dosage is 2 to 4 mcg per minute.

2.3 Drug Incompatibilities

Avoid contact with iron salts and alkalizing and oxidizing agents.

Whole blood or plasma, if indicated to increase blood volume, should be administered separately.

3 DOSAGE FORMS AND STRENGTHS

Injection: Norepinephrine is a clear, colorless sterile solution in the premixed, ready-to-use single dose intravenous infusion bags available as:

- 4 mg/250 mL (16 mcg/mL) of norepinephrine in 0.9% Sodium Chloride
- 8 mg/250 mL (32 mcg/mL) of norepinephrine in 0.9% Sodium Chloride
- 16 mg/250 mL (64 mcg/mL) of norepinephrine in 0.9% Sodium Chloride

4 CONTRAINDICATIONS

None.

5 WARNINGS AND PRECAUTIONS

5.1 Tissue Ischemia

Administration of Norepinephrine in Sodium Chloride Injection to patients who are hypotensive from hypovolemia can result in severe peripheral and visceral vasoconstriction, decreased renal perfusion and reduced urine output, tissue hypoxia, lactic acidosis, and reduced systemic blood flow despite “normal” blood pressure. Address hypovolemia prior to initiating Norepinephrine in Sodium Chloride Injection [see Dosage and Administration (2.1)]. Avoid Norepinephrine in Sodium Chloride Injection in patients with mesenteric or peripheral vascular thrombosis, as this may increase ischemia and extend the area of infarction.

Gangrene of the extremities has occurred in patients with occlusive or thrombotic vascular disease or who received prolonged or high dose infusions. Monitor for changes to the skin of the extremities in susceptible patients.

Extravasation of Norepinephrine in Sodium Chloride Injection may cause necrosis and sloughing of surrounding tissue. To reduce the risk of extravasation, infuse into a large vein, check the infusion site frequently for free flow, and monitor for signs of extravasation [see Dosage and Administration (2.1)].

Emergency Treatment of Extravasation

To prevent sloughing and necrosis in areas in which extravasation has occurred, infiltrate the ischemic area as soon as possible, using a syringe with a fine hypodermic needle with 5 to 10 mg of phentolamine mesylate in 10 mL to 15 mL of 0.9% Sodium Chloride Injection in adults.

Sympathetic blockade with phentolamine causes immediate and conspicuous local hyperemic changes if the area is infiltrated within 12 hours.

5.2 Hypotension after Abrupt Discontinuation

Sudden cessation of the infusion rate may result in marked hypotension. When discontinuing the infusion, gradually reduce the Norepinephrine in Sodium Chloride Injection infusion rate while expanding blood volume with intravenous fluids.

5.3 Cardiac Arrhythmias

Norepinephrine in Sodium Chloride Injection elevates intracellular calcium concentrations and may cause arrhythmias, particularly in the setting of hypoxia or hypercarbia. Perform continuous cardiac monitoring of patients with arrhythmias.

6 ADVERSE REACTIONS

The following adverse reactions are described in greater detail in other sections:

- Tissue Ischemia [see Warnings and Precautions (5.1)]
- Hypotension [see Warnings and Precautions (5.2)]
- Cardiac Arrhythmias [see Warnings and Precautions (5.3)]

The most common adverse reactions are hypertension and bradycardia.

The following adverse reactions can occur:

Nervous system disorders: Anxiety, headache

Respiratory disorders: Respiratory difficulty, pulmonary edema

7 DRUG INTERACTIONS

7.1 MAO-Inhibiting Drugs

Co-administration of Norepinephrine in Sodium Chloride Injection with monoamine oxidase (MAO) inhibitors or other drugs with MAO-inhibiting properties (e.g., linezolid) can cause severe, prolonged hypertension.

If administration of Norepinephrine in Sodium Chloride Injection cannot be avoided in patients who recently have received any of these drugs and in whom, after discontinuation, MAO activity has not yet sufficiently recovered, monitor for hypertension.

7.2 Tricyclic Antidepressants

Co-administration of Norepinephrine in Sodium Chloride Injection with tricyclic antidepressants (including amitriptyline, nortriptyline, protriptyline, clomipramine, desipramine, imipramine) can cause severe, prolonged hypertension. If administration of Norepinephrine in Sodium Chloride Injection cannot be avoided in these patients, monitor for hypertension.

7.3 Antidiabetics

Norepinephrine in Sodium Chloride Injection can decrease insulin sensitivity and raise blood glucose. Monitor glucose and consider dosage adjustment of antidiabetic drugs.

7.4 Halogenated Anesthetics

Concomitant use of Norepinephrine in Sodium Chloride Injection with halogenated anesthetics (e.g., cyclopropane, desflurane, enflurane, isoflurane, and sevoflurane) may lead to ventricular tachycardia or ventricular fibrillation. Monitor cardiac rhythm in patients receiving concomitant halogenated anesthetics.

8 USE IN SPECIFIC POPULATIONS

8.1 Pregnancy

Risk Summary

Limited published data consisting of a small number of case reports and multiple small trials involving the use of norepinephrine in pregnant women at the time of delivery have not identified an increased risk of major birth defects, miscarriage or adverse maternal or fetal outcomes. There are risks to the mother and fetus from hypotension associated with septic shock, myocardial infarction and stroke which are medical emergencies in pregnancy and can be fatal if left untreated (see Clinical Considerations). In animal reproduction studies, using high doses of intravenous norepinephrine resulted in lowered maternal placental blood flow. Clinical relevance to changes in the human fetus is unknown since the average maintenance dose is ten times lower (see Data). Increased fetal reabsorptions were observed in pregnant hamsters after receiving daily injections at approximately 2 times the maximum recommended dose on a mg/m^2 basis for four days during organogenesis (see Data).

The estimated background risk for major birth defects and miscarriage for the indicated population is unknown. All pregnancies have a background risk of birth defect, loss, or other adverse outcomes. In the U.S. general population, the estimated background risk of major birth defects and miscarriage in clinically recognized pregnancies is 2-4% and 15-20%, respectively.

Clinical Considerations

Disease-associated maternal and/or embryo/fetal risk

Hypotension associated with septic shock, myocardial infarction, and stroke are medical emergencies in pregnancy which can be fatal if left untreated. Delaying treatment in pregnant women with hypotension associated with septic shock, myocardial infarction and stroke may increase the risk of maternal and fetal morbidity and mortality. Life-sustaining therapy for the pregnant woman should not be withheld due to potential concerns regarding the effects of norepinephrine on the fetus.

Data

Animal Data

A study in pregnant sheep receiving high doses of intravenous norepinephrine (40 mcg/min, at approximately 10 times the average maintenance dose of 2-4 mcg/min in human, on a mg/kg basis) exhibited a significant decrease in maternal placental blood flow. Decreases in fetal oxygenation, urine and lung liquid flow were also observed.

Norepinephrine administration to pregnant rats on Gestation Day 16 or 17 resulted in cataract production in rat fetuses.

In hamsters, an increased number of resorptions (29.1% in study group vs. 3.4% in control group), fetal microscopic liver abnormalities and delayed skeletal ossification were observed at approximately 2 times the maximum recommended intramuscular or subcutaneous dose (on a mg/m^2 basis at a maternal subcutaneous dose of 0.5 mg/kg/day from Gestation Day 7-10).

8.2 Lactation

Risk Summary

There are no data on the presence of norepinephrine in either human or animal milk, the effects on the breastfed infant, or the effects on milk production. Clinically relevant exposure to the infant is not expected based on the short half-life and poor oral bioavailability of norepinephrine.

8.4 Pediatric Use

Safety and effectiveness in pediatric patients have not been established.

8.5 Geriatric Use

Clinical studies of Norepinephrine in Sodium Chloride Injection did not include sufficient numbers of subjects aged 65 and over to determine whether they respond differently from younger subjects. Other reported clinical experience has not identified differences in responses between the elderly and younger patients. In general, dose selection for an elderly patient should be cautious, usually starting at the low end of the dosing range, reflecting the greater frequency of decreased hepatic, renal, or cardiac function, and of concomitant disease or other drug therapy.

Avoid administration of Norepinephrine in Sodium Chloride Injection into the veins in the leg in elderly patients [see Warnings and Precautions (5.1)].

10 OVERDOSAGE

Overdosage with Norepinephrine in Sodium Chloride Injection may result in headache, severe hypertension, reflex bradycardia, marked increase in peripheral resistance, and decreased cardiac output.

In case of accidental overdosage, discontinue Norepinephrine in Sodium Chloride Injection until the condition of the patient stabilizes.

11 DESCRIPTION

Norepinephrine (sometimes referred to as l-arterenol/Levarterenol or l-norepinephrine) is a catecholamine which differs from epinephrine by the absence of a methyl group on the nitrogen atom.

Chemically, Norepinephrine Bitartrate is (-)-α-(aminomethyl)-3,4-dihydroxybenzyl alcohol tartrate (1:1) (salt) monohydrate (molecular weight 337.3 g/mol) and has the following structural formula:

Norepinephrine in Sodium Chloride Injection is a clear, colorless, single dose sterile solution supplied as a ready-to-use intravenous infusion bag for intravenous use and does not require further dilution. Each mL contains the equivalent of 16 or 32 or 64 micrograms of norepinephrine base supplied as 31.90 or 63.80 or 127.6 micrograms per mL of norepinephrine bitartrate monohydrate. In addition, each mL of solution contains 0.01 mg edetate disodium dihydrate as a metal chelator and 9.0 mg sodium chloride for isotonicity. It has a pH of 3.5 to 4.5.

12 CLINICAL PHARMACOLOGY

12.1 Mechanism of Action

Norepinephrine is a peripheral vasoconstrictor (alpha-adrenergic action) and an inotropic stimulator of the heart and dilator of coronary arteries (beta-adrenergic action).

12.2 Pharmacodynamics

The primary pharmacodynamic effects of norepinephrine are cardiac stimulation and vasoconstriction. Cardiac output is generally unaffected, although it can be decreased, and total peripheral resistance is also elevated. The elevation in resistance and pressure result in reflex vagal activity, which slows the heart rate and increases stroke volume. The elevation in vascular tone or resistance reduces blood flow to the major abdominal organs as well as to skeletal muscle. Coronary blood flow is substantially increased secondary to the indirect effects of alpha stimulation. After intravenous administration, a pressor response occurs rapidly and reaches steady state within 5 minutes. The pharmacologic actions of norepinephrine are terminated primarily by uptake and metabolism in sympathetic nerve endings. The pressor action stops within 1-2 minutes after the infusion is discontinued.

12.3 Pharmacokinetics

Absorption

Following intravenous administration, the steady state plasma concentration is achieved in 5 min.

Distribution

Plasma protein binding of norepinephrine is approximately 25%. It is mainly bound to plasma albumin and to a smaller extent to prealbumin and alpha 1-acid glycoprotein. The volume of distribution is 8.8 L. Norepinephrine localizes mainly in sympathetic nervous tissue. It crosses the placenta but not the blood-brain barrier.

Elimination

The mean half-life of norepinephrine is approximately 2.4 min. The average metabolic clearance is 3.1 L/min.

Metabolism

Norepinephrine is metabolized in the liver and other tissues by a combination of reactions involving the enzymes catechol-O-methyltransferase (COMT) and MAO. The major metabolites are normetanephrine and 3-methoxy-4-hydroxy mandelic acid (vanillylmandelic acid, VMA), both of which are inactive. Other inactive metabolites include 3-methoxy-4-hydroxyphenylglycol, 3,4-dihydroxymandelic acid, and 3,4-dihydroxyphenylglycol.

Excretion

Noradrenaline metabolites are excreted in urine primarily as sulphate conjugates and, to a lesser extent, as glucuronide conjugates. Only small quantities of norepinephrine are excreted unchanged.

13 NONCLINICAL TOXICOLOGY

13.1 Carcinogenesis, Mutagenesis, Impairment of Fertility

Carcinogenesis, mutagenesis, and fertility studies have not been performed.

16 HOW SUPPLIED/STORAGE AND HANDLING

Norepinephrine in Sodium Chloride Injection (norepinephrine bitartrate) is supplied as a clear, colorless sterile solution in a 250 mL non-PVC infusion bag with single function connector system consisting of a port and cap, packaged individually in an aluminum foil pouch with an oxygen scavenger. Supplied as:

Unit of Sale | Concentration | Package Size
NDC 81298-9659-3 | 4 mg/250 mL (16 mcg/mL) | 10 bags
NDC 81298-9655-3 | 8 mg/250 mL (32 mcg/mL) | 10 bags
NDC 81298-9658-3 | 16 mg/250 mL (64 mcg/mL) | 10 bags

Store at 20°C to 25°C (68°F to 77°F); excursions permitted to 15°C to 30°C (59°F to 86°F). [See USP Controlled Room Temperature.] Protect from light. Once the overwrap is removed, the bag can be stored at room temperature for up to 45 days.

17 PATIENT COUNSELING INFORMATION

Risk of Tissue Damage

Advise the patient, family, or caregiver to report signs of extravasation urgently [see Warnings and Precautions (5.1)].

Manufactured for:
Long Grove Pharmaceuticals, LLC
Rosemont, IL 60018

Rev. 10/2024

076273002 R01

Principal Display Panel – 4 mg Pouch Label

NDC: 81298-9659-1
Rx only
1 x 250 mL

Norepinephrine
in 0.9% Sodium Chloride injection

4 mg per 250 mL
(16 mcg/mL)

Keep in sealed overwrap until time of use.

LONG GROVE
PHARMACEUTICALS™

Principal Display Panel – 8 mg Pouch Label

NDC: 81298-9655-1
Rx only
1 x 250 mL

Norepinephrine
in 0.9% Sodium Chloride injection

8 mg per 250 mL
(32 mcg/mL)

Keep in sealed overwrap until time of use.

LONG GROVE
PHARMACEUTICALS™

Principal Display Panel – 16 mg Pouch Label

NDC: 81298-9658-1
Rx only
1 x 250 mL

Norepinephrine
in 0.9% Sodium Chloride injection

16 mg per 250 mL
(64 mcg/mL)

Keep in sealed overwrap until time of use.

LONG GROVE
PHARMACEUTICALS™